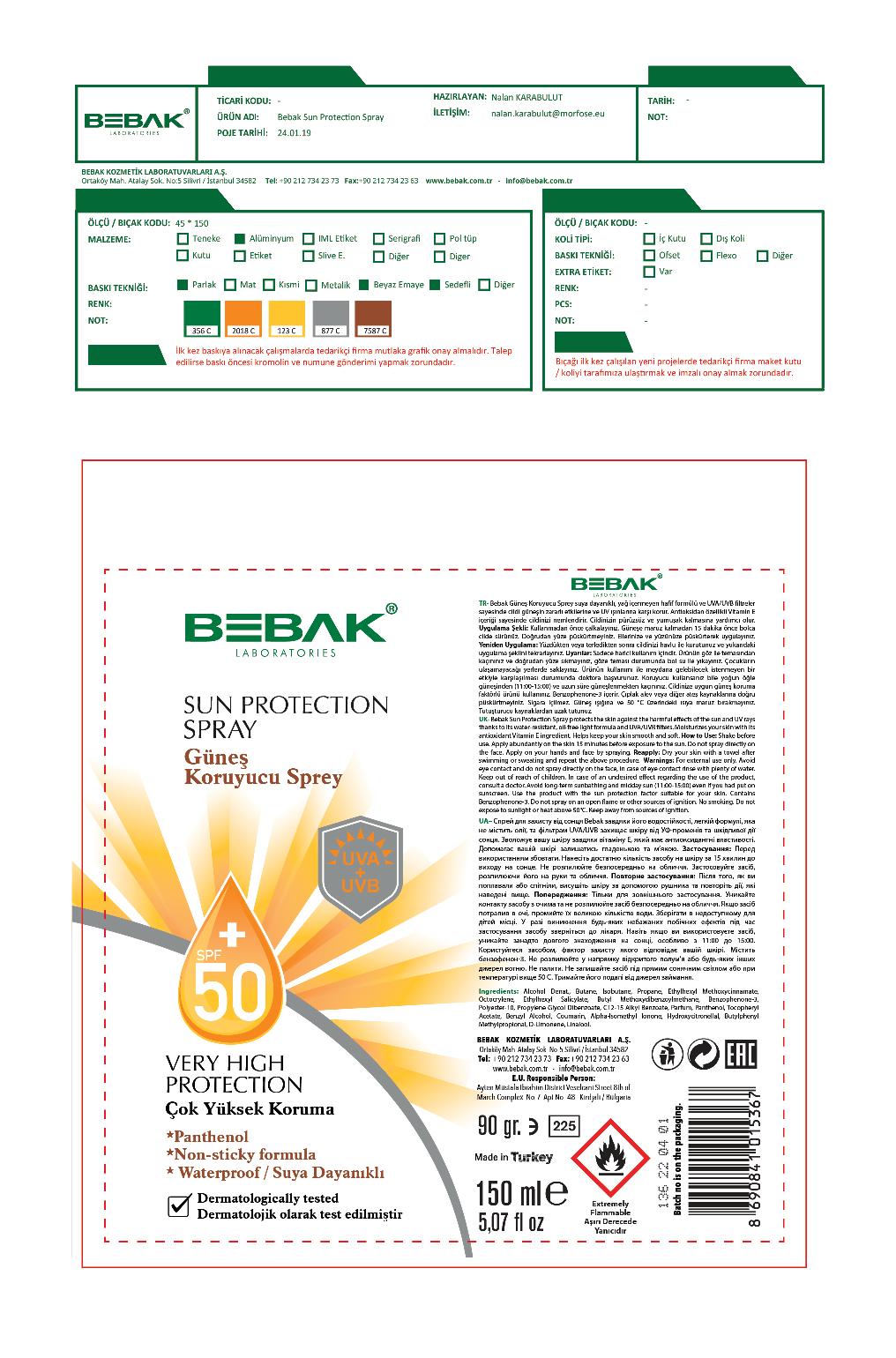 DRUG LABEL: Bebak Sun Protection
NDC: 77462-008 | Form: SPRAY
Manufacturer: SORA KOZMETIK SANAYI TICARET ANONIM SIRKETI
Category: otc | Type: HUMAN OTC DRUG LABEL
Date: 20200716

ACTIVE INGREDIENTS: OCTINOXATE 10.5 g/150 g
INACTIVE INGREDIENTS: ISOBUTANE; HYDROXYCITRONELLAL; BUTYLPHENYL METHYLPROPIONAL; ALKYL (C12-15) BENZOATE; BUTANE; AVOBENZONE; OXYBENZONE; ALPHA-TOCOPHEROL ACETATE; OCTISALATE; ALCOHOL; COUMARIN; PROPYLENE GLYCOL DIBENZOATE; PANTHENOL; LIMONENE, (+)-; LINALOOL, (+)-; PROPANE; OCTOCRYLENE; ISOMETHYL-.ALPHA.-IONONE; POLYESTER-10; BENZYL ALCOHOL

Bebak Sun Protection Spray

Active Ingredient

Ethylhexyl Methoxycinnamate ....7%

Purpose

Sunscreen

Uses

Protects the skin against the harmful effects of the sun and UV rays

Warnings

For external use only.

In case of an undesired effect regarding the use of this product, consult a doctor. Avoid long-term sunbathin and midday sun even if you had put on sunscreen. Use the product with the sun protectinos factor suitable for your skin.

Contains Benzophenone-3. Do no spray on an open flame or other sources of igniatino. No smoking. Do not expose to sunlight or heat above 50 degrees C. Keep away from sources of ignition.

WHEN USING

Avoid eye contact and do not spray directly on the face. In case of eye contact rinse with plenty of water.

Keep out of reach of children.

Directions

Shake before use. Apply on your hands and face by spraying. Dry your skin with a towel after swimming or sweating and repeat.

Inactive Ingredients

Alcohol Denat. Butane, Isobutane, propane, octocrylene, ethylhexyl salicylate, butyl methoxydibenzoylmethane, benzophenone-3, polyester-10, propylene glycol dibenzoate, c12-c15 alkyl benzoate, parfum, panthenol, tocopheryl acetate, benzyl alcohol, coumarin, alpha-isomethyl ionone, hydroxycitronellal, butylphenyl methylpropioinal, d-limonene, linalool.

Inactive Ingredients

Alcohol Denat. Butane, Isobutane, propane, octocrylene, ethylhexyl salicylate, butyl methoxydibenzoylmethane, benzophenone-3, polyester-10, propylene glycol dibenzoate, c12-c15 alkyl benzoate, parfum, panthenol, tocopheryl acetate, benzyl alcohol, coumarin, alpha-isomethyl ionone, hydroxycitronellal, butylphenyl methylpropioinal, d-limonene, linalool.